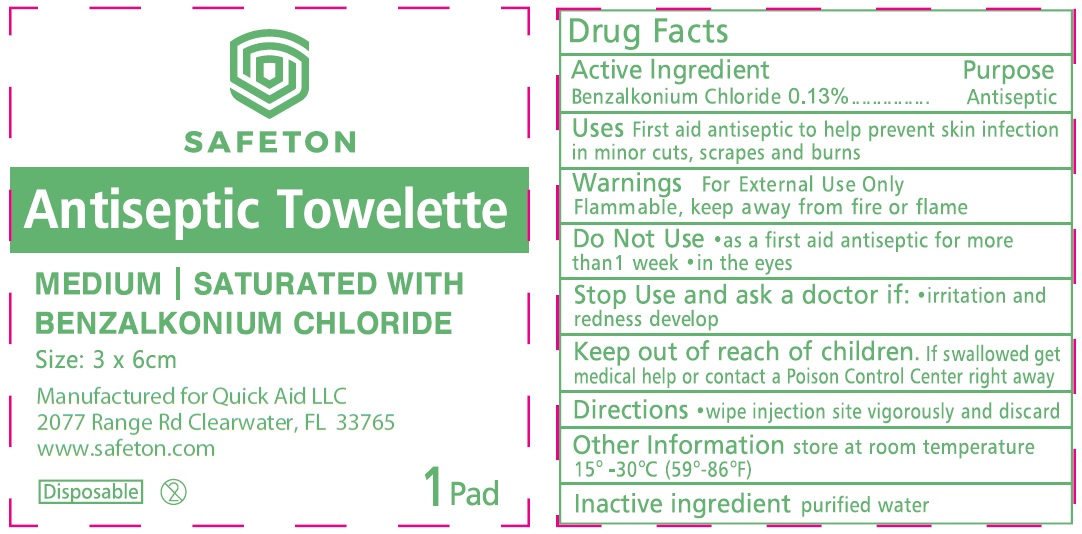 DRUG LABEL: Safeton Antiseptic Towelette Benzalkonium Chloride
NDC: 83006-002 | Form: SWAB
Manufacturer: QUICK AID LLC
Category: otc | Type: HUMAN OTC DRUG LABEL
Date: 20221019

ACTIVE INGREDIENTS: BENZALKONIUM CHLORIDE 1.3 mg/1 g
INACTIVE INGREDIENTS: WATER

Safeton Antiseptic Towelette Benzalkonium Chloride

Active Ingredient

Benzalkonium Chloride 0.13%

Purpose

Antiseptic

Use

First aid antiseptic to help prevent skin infection in minor cuts, scrapes and burns

Warnings

For External Use Only

Flammable, keep away from fire or flame

Do Not Use

- as a first aid antiseptic for more than 1 week
- in the eyes

Stop Use and ask a doctor if:

- irritation and redness develops

Keep out of reach of children.

If swallowed get medical help or contact a Poison Control Center right away

Directions

- wipe injection site vigorously and discard

Other Information

- store at room temperature 15°-30°C (59°-86°F)

Inactive ingredients

- purified water